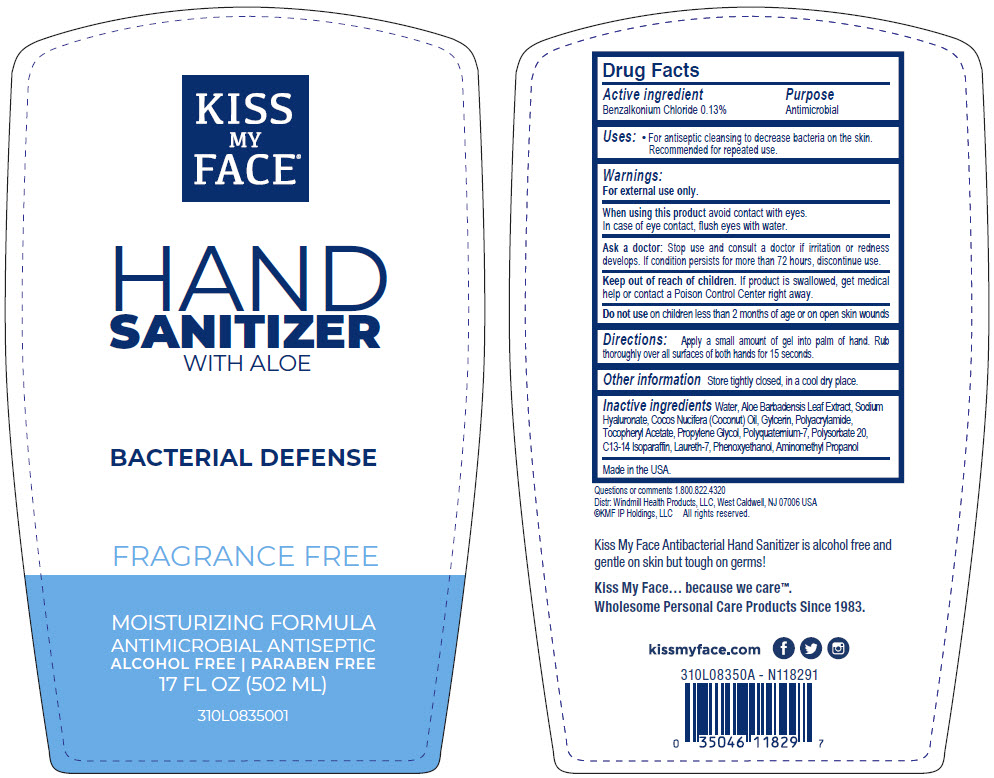 DRUG LABEL: Kiss My Face Hand Sanitizer with Aloe Bacterial Defense Fragrance Free
NDC: 74154-006 | Form: LIQUID
Manufacturer: Windmill Health Products, LLC
Category: otc | Type: HUMAN OTC DRUG LABEL
Date: 20220204

ACTIVE INGREDIENTS: BENZALKONIUM CHLORIDE 130 mg/100 mL
INACTIVE INGREDIENTS: WATER; ALOE VERA LEAF; HYALURONATE SODIUM; COCONUT OIL; GLYCERIN; .ALPHA.-TOCOPHEROL ACETATE; PROPYLENE GLYCOL; POLYQUATERNIUM-7 (70/30 ACRYLAMIDE/DADMAC; 1600000 MW); POLYSORBATE 20; C13-14 ISOPARAFFIN; LAURETH-7; PHENOXYETHANOL; AMINOMETHYLPROPANOL

Kiss My Face® Hand Sanitizer with Aloe Bacterial Defense Fragrance Free

Drug Facts

Active ingredient

Benzalkonium Chloride 0.13%

Purpose

Antimicrobial

Uses

- For antiseptic cleansing to decrease bacteria on the skin. Recommended for repeated use.

Warnings

For external use only.

When using this product avoid contact with eyes. In case of eye contact, flush eyes with water.

Ask a doctor

Stop use and consult a doctor if irritation or redness develops. If condition persists for more than 72 hours, discontinue use.

Keep out of reach of children. If product is swallowed, get medical help or contact a Poison Control Center right away.

Do not use on children less than 2 months of age or on open skin wounds

Directions

Apply a small amount of gel into palm of hand. Rub thoroughly over all surfaces of both hands for 15 seconds.

Other information

Store tightly closed, in a cool dry place.

Inactive ingredients

Water, Aloe Barbadensis Leaf Extract, Sodium Hyaluronate, Cocos Nucifera (Coconut) Oil, Gylcerin, Polyacrylamide, Tocopheryl Acetate, Propylene Glycol, Polyquaternium-7, Polysorbate 20, C13-14 Isoparaffin, Laureth-7, Phenoxyethanol, Aminomethyl Propanol

Questions or comments

1.800.822.4320

Made in the USA.

PRINCIPAL DISPLAY PANEL - 502 ML Bottle Label

KISS
MY
FACE®

HAND
SANITIZER
WITH ALOE

BACTERIAL DEFENSE

FRAGRANCE FREE

MOISTURIZING FORMULA
ANTIMICROBIAL ANTISEPTIC
ALCOHOL FREE | PARABEN FREE
17 FL OZ (502 ML)

310L0835001